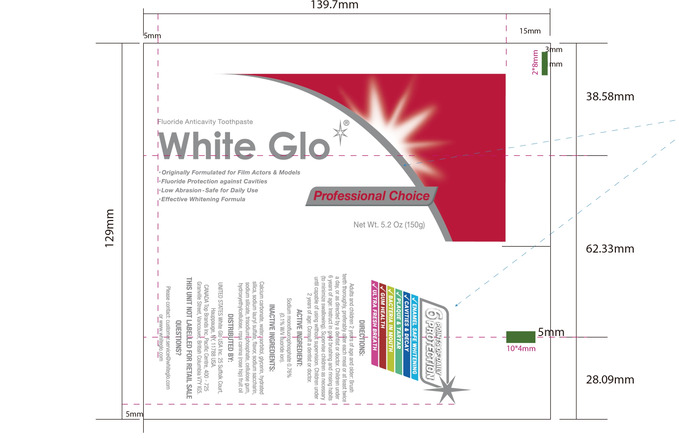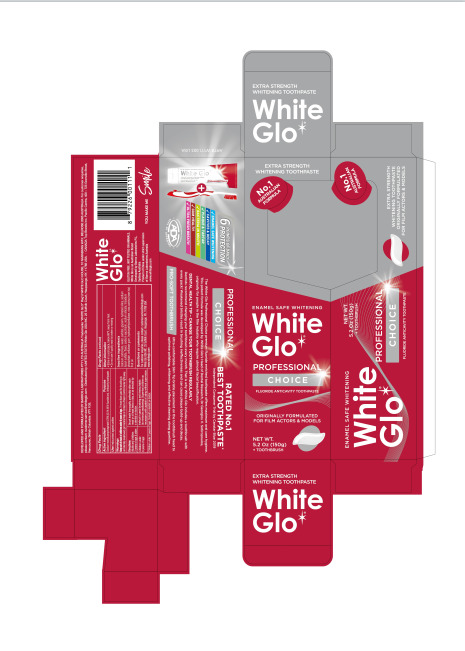 DRUG LABEL: Professional Choice
NDC: 82168-003 | Form: PASTE, DENTIFRICE
Manufacturer: Guangzhou City Caiye Cosmetics CO., Ltd
Category: otc | Type: HUMAN OTC DRUG LABEL
Date: 20241201

ACTIVE INGREDIENTS: SODIUM MONOFLUOROPHOSPHATE 0.76 g/100 g
INACTIVE INGREDIENTS: CALCIUM CARBONATE; AQUA; GLYCERIN; SORBITOL; SILICA; SODIUM LAURYL SULFATE; SODIUM SACCHARIN; SODIUM SILICATE; CELLULOSE GUM; HYDROXYETHYLCELLULOSE

82168-003

Active Ingredient(s)

Sodium monofluorophosphate 0.76%

Purpose

Anticavity toothpaste

Use

Use helps protect against cavities

Warnings

Keep out of reach of children under 6years of age. If more than used for brushing is
acidenaly sallowed, get medicalhelp or contact aPoisonControl Center right away.

Do not use on open skin wounds

WHEN USING

Please keep away from your eyes when using this product

STOP USE

If in contact with the eyes, rinse thoroughly with water.

Keep out of reach of children under 6 years of age.

Directions

Adults and children 2 years of age & older: Brush teeth thoroughly, preferably after each meal or at least twice a day, or as directed by
a dentist or doctor.
Children under 6 years of age: Instruct in good brushing and rinsing habits (to minimize swallowing). Supervise children as
necessary until capable of using without supervision.
Children under 2 years of age: Consult a dentist or doctor.

Other information

●Store in a cool place, below 86°F, away from heat
●Do not use if quality seal is broken or missing

Inactive ingredients

Calcium carbonate, water, sorbitol, glycerin, hydrated silica, sodium lauryl sulfate, flavor, sodium saccharin, sodium silicate, trisodium
phosphate, cellulose gum, hydroxyethylcellulose, rosa canina (rose hip) fruit oil